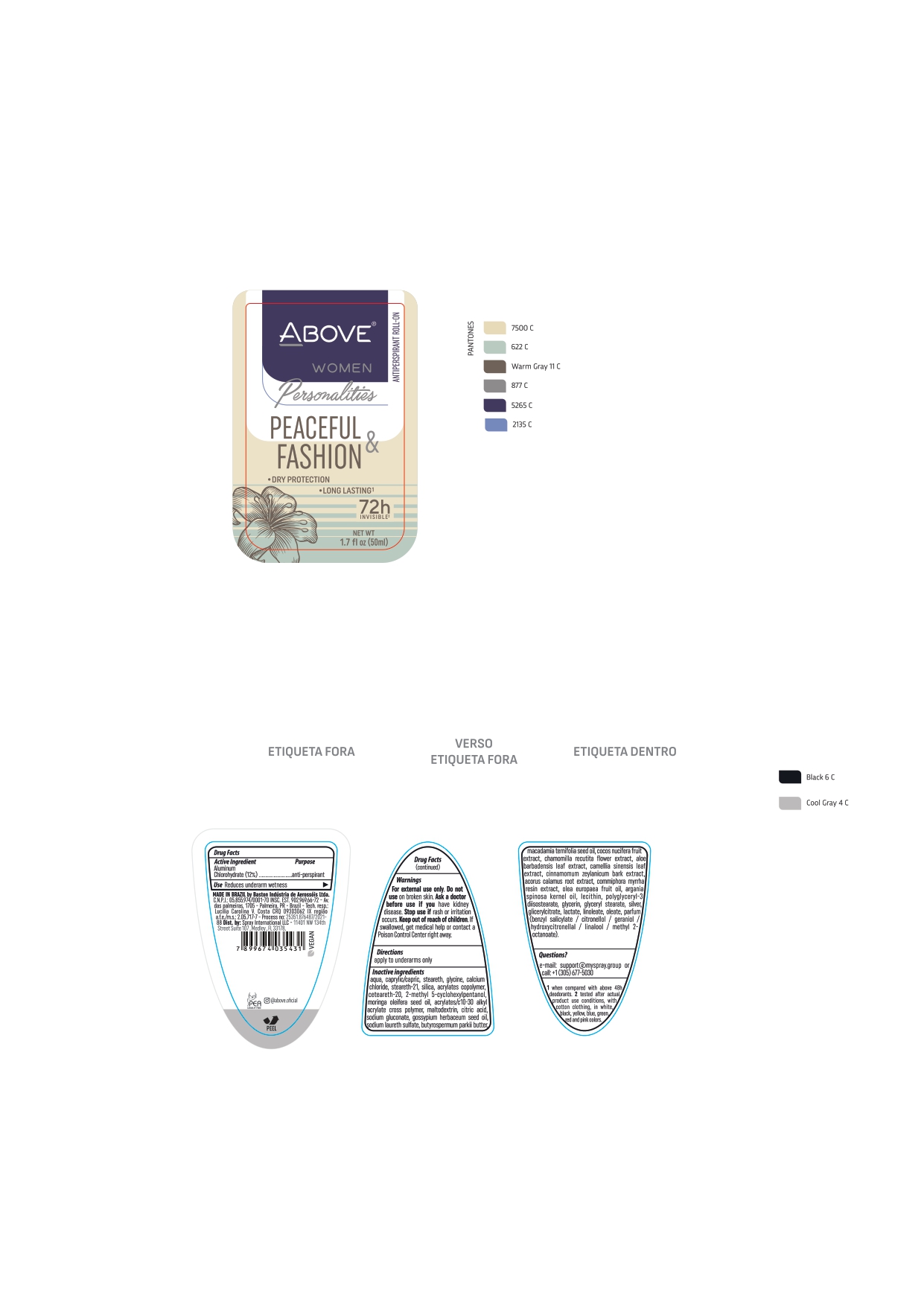 DRUG LABEL: ABOVE WOMEN PERSONALITIES PEACEFUL and FASHION
NDC: 73306-1134 | Form: CREAM
Manufacturer: BASTON INDUSTRIA DE AEROSSOIS LTDA
Category: otc | Type: HUMAN OTC DRUG LABEL
Date: 20221114

ACTIVE INGREDIENTS: ALUMINUM CHLOROHYDRATE 12 mg/100 g
INACTIVE INGREDIENTS: MEDIUM-CHAIN TRIGLYCERIDES

ABOVE WOMEN PERSONALITIES PEACEFUL & FASHION

ALUMINUM CHLOROHYDRATE 12 %